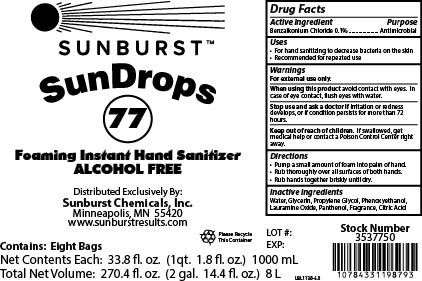 DRUG LABEL: SunDrops 77
NDC: 63621-354 | Form: SOAP
Manufacturer: Sunburst Chemicals, Inc.
Category: otc | Type: HUMAN OTC DRUG LABEL
Date: 20251111

ACTIVE INGREDIENTS: BENZALKONIUM CHLORIDE 1 mg/1 mL
INACTIVE INGREDIENTS: PANTHENOL; PHENOXYETHANOL; CITRIC ACID MONOHYDRATE; WATER; PROPYLENE GLYCOL; LAURAMINE OXIDE; GLYCERIN

SunDrops 77

Active Ingredient

Benzalkonium Chloride 0.1%

Purpose

Antimicrobial

Uses

- For hand sanitizing to decrease bacteria on the skin
- Recommended for repeated use

Warnings

For external use only.

When using this product avoid contact with eyes. In case of eye contact, flush eyes with water.

Stop use and ask a doctor if irritation or redness develops, or if condition persists for more than 72 hours.

Keep out of reach of children. If swallowed, get medical help or contact a Poison Control Center right away.

Directions

- Pump a small amount of foam into palm of hand.
- Rub thoroughly over all surfaces of both hands.
- Rub hands together briskly until dry.

Inactive Ingredients

Water, Glycerin, Propylene Glycol, Phenoxyethanol, Lauramine Oxide, Panthenol, Fragrance, Citric Acid